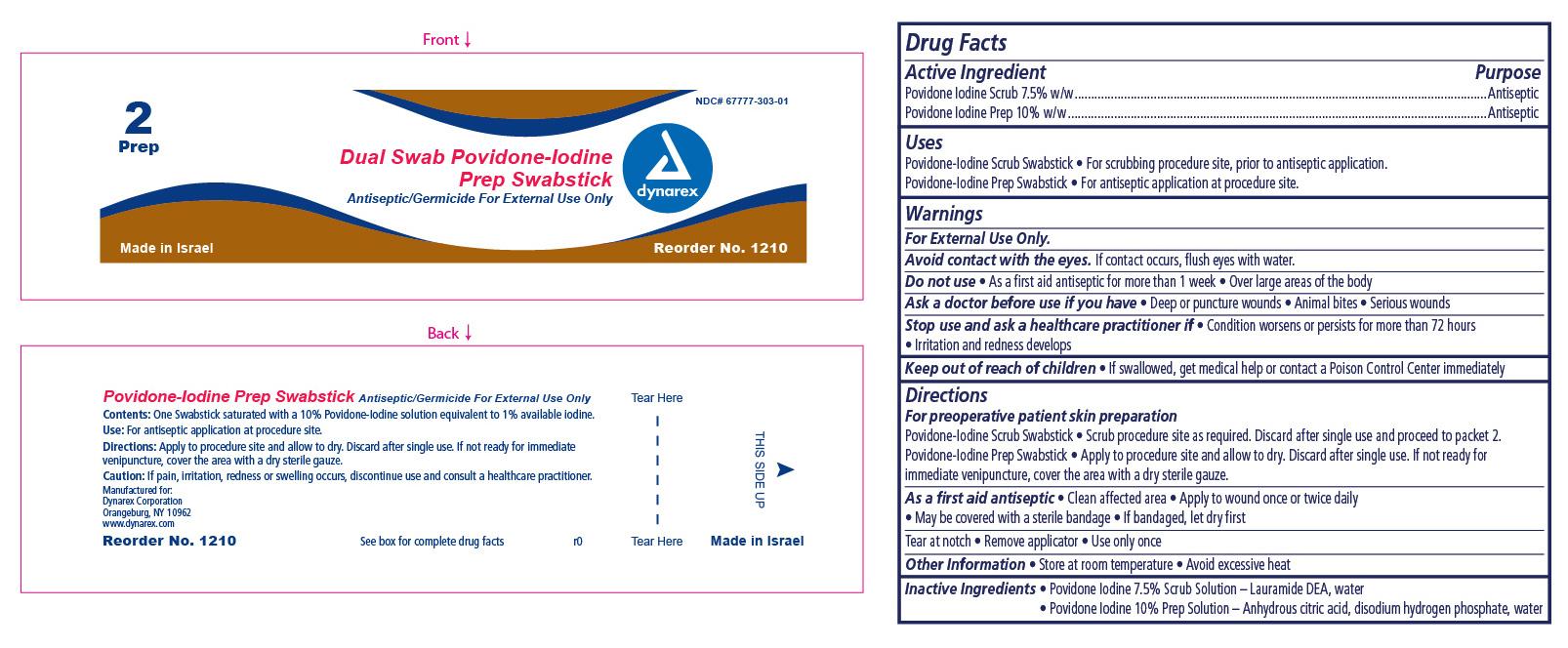 DRUG LABEL: Dual Swab Scrub Swabstick
NDC: 67777-303 | Form: SWAB
Manufacturer: Dynarex Corporation
Category: otc | Type: HUMAN OTC DRUG LABEL
Date: 20151104

ACTIVE INGREDIENTS: POVIDONE-IODINE 10 g/100 g
INACTIVE INGREDIENTS: ANHYDROUS CITRIC ACID; SODIUM PHOSPHATE, DIBASIC ANHYDROUS; WATER

Dual Swab Povidone Iodine Prep Swabstick

Active Ingredient

Active ingredient Purpose

Povidone iodine 10% Antiseptic

Purpose

For antiseptic application at procedure site.

Indications and usage

For pre-operative patient skin preparation.

Warnings

For External Use Only

Avoid contact with the eyes. If contact occurs, flush with water.

Stop use

Stop use and ask a healthcare professional if,

- condition worsens or persists for more than 72 hours
- if pain, irritation, redness or swelling occurs

Ask a doctor before use if you have

- deep puncture wounds
- animal bites
- serious wounds

Do not use

- as a first aid antiseptic for more than 1 week
- over large areas of the body

Keep out of reach of children

- if swallowed, get medical help or contact a Poison Control Center immediately.

Dosage and administration

Directions

For preoperative patient skin preparation:

- Apply to procedure siteand allow to dry. Discard after single use.If not ready for immediate venipuncture, cover the area with a dry sterile gauze.

As a first aid antiseptic:

- clean affected area
- apply to wound once or twice daily
- may be covered with a sterile bandage
- if bandaged, let dry first.

Tear at notch, remove applicator, use only once.

Inactive ingredients

Anhydrous citric acid, disodium hydrogen phosphate, Water

Other information

- Store at room temperature
- Avoid excessive heat

Principal Display Panel

Dynarex Dual Swab Povidone Iodine Prep Swabstick

Item #: 1210

1210 Prep.jpg